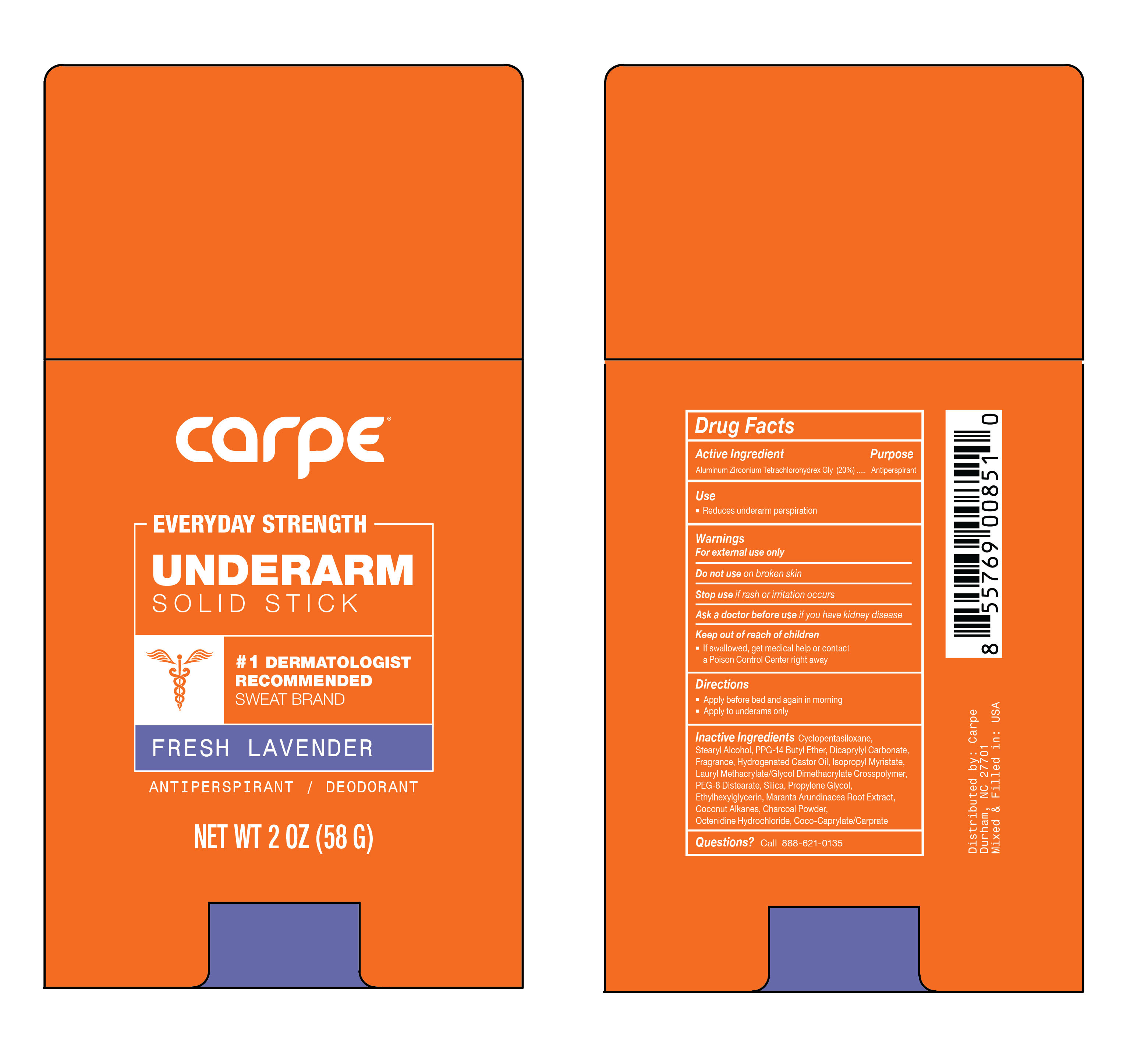 DRUG LABEL: Everyday Strength Underarm Antiperspirant Fresh Lavender
NDC: 74307-012 | Form: STICK
Manufacturer: Clutch Inc
Category: otc | Type: HUMAN OTC DRUG LABEL
Date: 20220509

ACTIVE INGREDIENTS: ALUMINUM ZIRCONIUM TETRACHLOROHYDREX GLY 20 g/100 g
INACTIVE INGREDIENTS: PROPYLENE GLYCOL; COCONUT ALKANES; OCTENIDINE HYDROCHLORIDE; COCOYL CAPRYLOCAPRATE; PPG-14 BUTYL ETHER; CYCLOMETHICONE 7; STEARYL ALCOHOL; DICAPRYLYL CARBONATE; HYDROGENATED CASTOR OIL; LAURYL METHACRYLATE/GLYCOL DIMETHACRYLATE CROSSPOLYMER; PEG-8 DISTEARATE; SILICON DIOXIDE; ISOPROPYL MYRISTATE; ACTIVATED CHARCOAL; ETHYLHEXYLGLYCERIN; MARANTA ARUNDINACEA ROOT

Everyday Strength Underarm Antiperspirant Fresh Lavender

Active Ingredient Purpose

Aluminum Zirconium Tetrachlorohydrex Gly...Antiperspirant

Use

- Reduces underarm perspiration

Keep out reach of children

- If swallowed, get medical help or contact a Poison Control Center right away

Stop use if rash or irritation occurs

Warnings

For external use only

Do not use on broken skin

Ask a doctor before use if you have kidney disease

Directions

- Apply before bed and again in the morning
- Apply to underarms only

INACTIVE INGREDIENT

Inactive Ingredients Cyclopentasiloxane, Stearyl Alcohol, PPG-14 Butyl Ether, Dicaprylyl Carbonate, Fragrance, Hydrogenated Castor Oil, Isopropyl Myristate, Lauryl Methacrylate/Glycol Dimethacrylate Crosspolymer, PEG-8 Distearate, Silica, Propylene Glycol, Ethylhexylglycerin, Maranta Arundinacea Root Extract, Coconut Alkanes, Charcoal Powder, Octenidine Hydrochloride, Coco-Caprylate/Caprate

PACKAGE LABEL

carpe

Everyday Strength

Underarm Solid Stick

Fresh Lavender

Antiperspirant / Deodorant

NET WT 2 OZ (58 G)